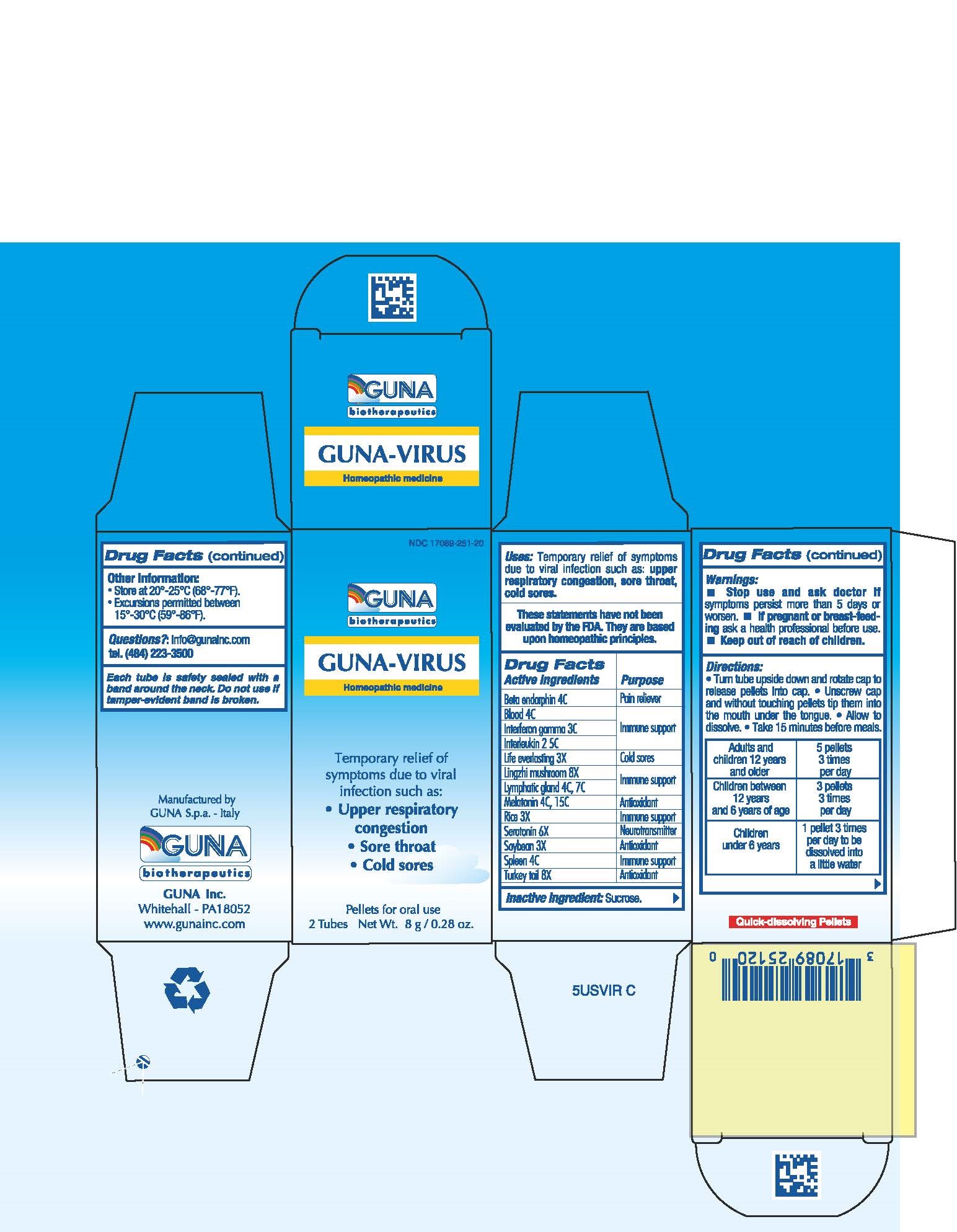 DRUG LABEL: GUNA-VIRUS
NDC: 17089-251 | Form: PELLET
Manufacturer: Guna spa
Category: homeopathic | Type: HUMAN OTC DRUG LABEL
Date: 20221114

ACTIVE INGREDIENTS: ALDESLEUKIN 5 [hp_C]/4 g; EVERLASTING EXTRACT 3 [hp_X]/4 g; FOMITOPSIS PINICOLA FRUITING BODY 8 [hp_X]/4 g; INTERFERON GAMMA-1B 3 [hp_C]/4 g; METENKEFALIN 4 [hp_C]/4 g; REISHI 8 [hp_X]/4 g; BROWN RICE 3 [hp_X]/4 g; SEROTONIN 6 [hp_X]/4 g; SOYBEAN 3 [hp_X]/4 g; SUS SCROFA BLOOD 4 [hp_C]/4 g; SUS SCROFA SPLEEN 4 [hp_C]/4 g; MELATONIN 15 [hp_C]/4 g; SUS SCROFA SMALL INTESTINE MUCOSA LYMPH FOLLICLE 7 [hp_C]/4 g
INACTIVE INGREDIENTS: SUCROSE 3.5 g/4 g

GUNA-VIRUS

ACTIVE INGREDIENTS/PURPOSE

BETA ENDORPHIN 4C PAIN RELIEVER
BLOOD 4C IMMUNE SUPPORT
INTERFERON GAMMA 3C IMMUNE SUPPORT
INTERLEUKIN 2 5C IMMUNE SUPPORT
LIFE EVERLASTING 3X COLD SORES
LING CHIN MUSHROOM 8X IMMUNE SUPPORT
LYMPHATIC GLAND 4C 7C IMMUNE SUPPORT
MELATONIN 4C 15C ANTIOXIDANT
RICE 3X IMMUNE SUPPORT
SEROTONIN 6X NEUROTRANSMITTER
SOYBEAN 3X ANTIOXIDANT
SPLEEN 4C IMMUNE SUPPORT
TURKEY TAIL 8X ANTIOXIDANT

USES

Temporary relief of symptoms due to viral infection such as:

- Upper respiratory congestion
- Sore throat
- Cold sores

WARNINGS

- Stop use and ask doctor if symptoms persist more than 5 days or worsen.
- If pregnant or breast-feeding ask a health professional before use.
- Keep out of reach of children.

PREGNANCY

If pregnant or breast-feeding ask a health professional before use.

WARNINGS

Keep out of reach of children

DIRECTIONS

- Turn tube upside down and rotate cap to release pellets into cap.
- Unscrew cap and without touching pellets tip them into the mouth under the tongue.
- Allow to dissolve
- Take 15 minutes before meals.

QUESTIONS

Questions?: info@gunainc.com
tel. (484) 223-3500

DOSAGE AND ADMINISTRATION

Adults and children twelve years and older: 5 pellets 3 times per day

Children between 12 years and 6 years of age: 3 pellets 3 times per day

Children under 6 years: 1 pellet 3 times per day to be dissolved into a little water

Inactive ingredient: Sucrose.